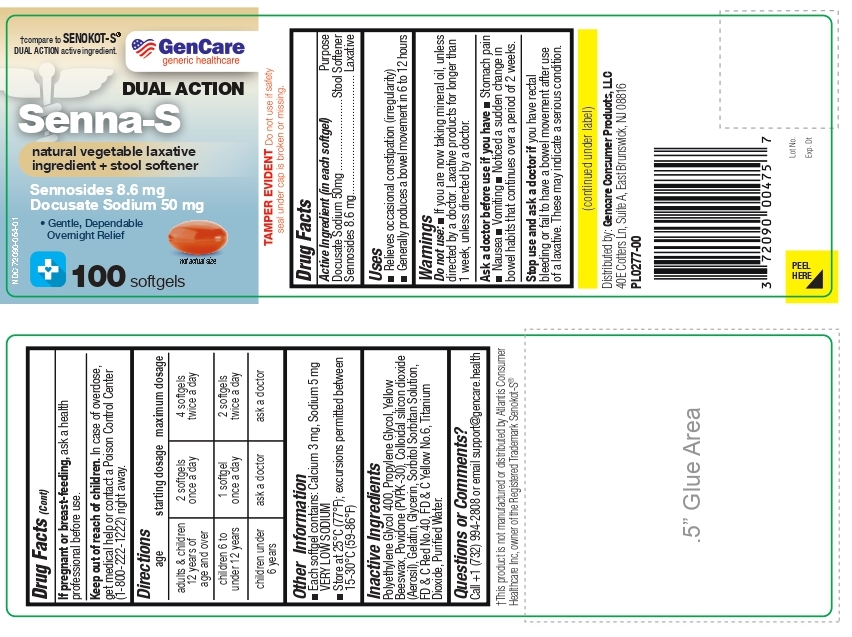 DRUG LABEL: Gencare-Senna-S Softgel
NDC: 72090-054 | Form: CAPSULE, LIQUID FILLED
Manufacturer: Pioneer Life Sciences, LLC
Category: otc | Type: HUMAN OTC DRUG LABEL
Date: 20250630

ACTIVE INGREDIENTS: DOCUSATE SODIUM 50 mg/1 1; SENNOSIDES 8.6 mg/1 1
INACTIVE INGREDIENTS: POLYETHYLENE GLYCOL 400; PROPYLENE GLYCOL; YELLOW WAX; POVIDONE K30; SILICON DIOXIDE; Gelatin; Glycerin; SORBITOL SOLUTION; SORBITAN; FD&C RED NO. 40; FD&C YELLOW NO. 6; Titanium Dioxide; WATER

Active Ingredient (in each softgel)

Docusate Sodium 50 mg

Sennosides 8.6 mg

Purpose

Docusate Sodium............... Stool softener

Sennosides........................Laxative

Uses:

- Relieves occasional constipation (irregularity).
- Generally produces a bowel movement in 6 to 12 hours.

Warnings:

Do not use: If you are now taking mineral oil, unless directed by a doctor. Laxative products for longer than 1 week, unless directed by a doctor.

Ask a doctor before use if you have:

- Stomach pain
- nausea
- vomiting
- Noticed a sudden change in bowel habits that continues over a period of 2 weeks.

Stop use and ask a doctor if you have:

- Rectal bleeding or fail to have a bowel movement after use of a laxative. These may indicate a serious condition.

PREGNANCY OR BREAST FEEDING

- If pregnant or breast-feeding, ask a health professional before use.

KEEP OUT OF REACH OF CHILDREN. In case of overdose, get medical help or contact a Poison Control Center (1-800-222-1222) right away.

DIRECTIONS

age | starting dosage | maximum dosage
adults & children 12 years of age and over | 2 softgels once a day | 4 softgels twice a day
children 6 to under 12 years | 1 softgel once a day | 2 softgels twice a day
children under 6 years | ask a doctor | ask a doctor

OTHER INFORMATION

- Each softgel contains: Calcium 3 mg, Sodium 5 mg VERY LOW SODIUM
- store at 25°C (77°F) excursions permitted between15°-30°C (59°-86°F)

INACTIVE INGREDIENTS

Polyethylene Glycol 400, Propylene Glycol, Yellow Beeswax, Povidone (PVPK-30), Colloidal silicon dioxide (Aerosil), Gelatin, Glycerin, Sorbitol Sorbitan Solution, FD & C Red No.40, FD & C Yellow No.6, Titanium Dioxide, Purified Water.

QUESTIONS OR COMMENTS?

Call +1 (732) 994-2808 or email support@gencare.health